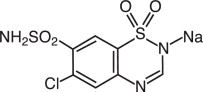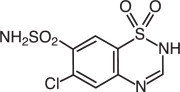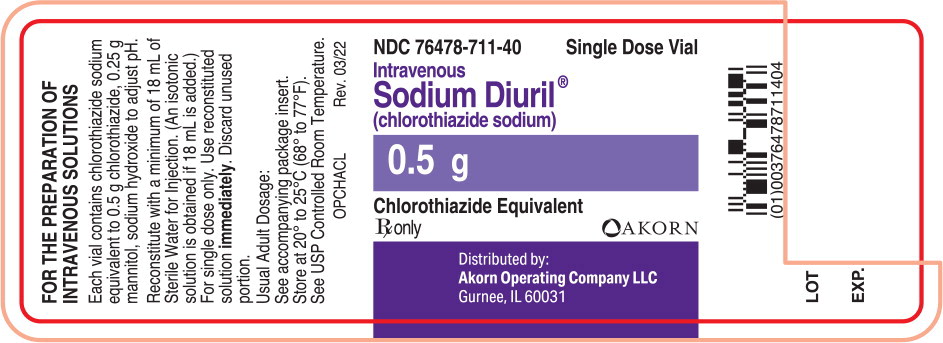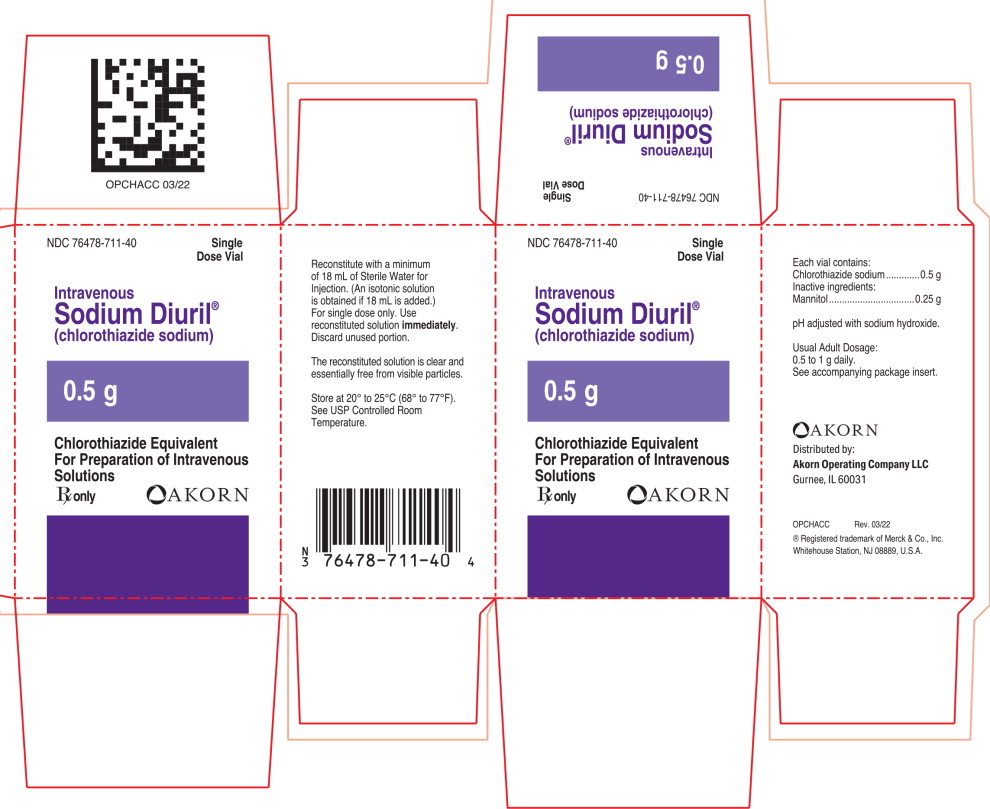 DRUG LABEL: Sodium Diuril
NDC: 76478-711 | Form: INJECTION
Manufacturer: Akorn
Category: prescription | Type: HUMAN PRESCRIPTION DRUG LABEL
Date: 20220701

ACTIVE INGREDIENTS: chlorothiazide sodium 0.5 mg/18 mL
INACTIVE INGREDIENTS: mannitol; sodium hydroxide

Intravenous
Sodium Diuril®
(chlorothiazide sodium)

Rx only

DESCRIPTION

Intravenous Sodium DIURIL (chlorothiazide sodium) is a diuretic and antihypertensive. It is 6-chloro-2H-1,2,4-benzothiadiazine-7-sulfonamide 1,1-dioxide monosodium salt and its molecular weight is 317.71.

Its empirical formula is C7H5ClN3NaO4S2 and its structural formula is:

Intravenous Sodium DIURIL is a sterile lyophilized white powder and is supplied in a vial containing:

Chlorothiazide sodium equivalent to chlorothiazide . . . . . . . . . . . . . . . . . . . . . . . . . . . . . . . . . . . . . . . . . . . . . . . 0.5 g

Inactive ingredients: Mannitol . . . . . . . . . . . . . . . . . . . . . . . . . . . . . . . . . . . . . . . . . . . . . . . . . . . . . . . . . . . . . . . . . 0.25 g

Sodium hydroxide to adjust pH.

DIURIL (chlorothiazide) is a diuretic and antihypertensive. It is 6-chloro-2H-1,2,4-benzothiadiazine-7-sulfonamide 1,1-dioxide. Its empirical formula is C7H6ClN3O4S2 and its structural formula is:

It is a white, or practically white, crystalline powder with a molecular weight of 295.72, which is very slightly soluble in water, but readily soluble in dilute aqueous sodium hydroxide. It is soluble in urine to the extent of about 150 mg per 100 mL at pH 7.

CLINICAL PHARMACOLOGY

The mechanism of the antihypertensive effect of thiazides is unknown. DIURIL (chlorothiazide) does not usually affect normal blood pressure.

DIURIL (chlorothiazide) affects the distal renal tubular mechanism of electrolyte reabsorption. At maximal therapeutic dosage all thiazides are approximately equal in their diuretic efficacy.

DIURIL (chlorothiazide) increases excretion of sodium and chloride in approximately equivalent amounts. Natriuresis may be accompanied by some loss of potassium and bicarbonate.

After oral use diuresis begins within 2 hours, peaks in about 4 hours and lasts about 6 to 12 hours. Following intravenous use of Sodium DIURIL, onset of the diuretic action occurs in 15 minutes and the maximal action in 30 minutes.

Pharmacokinetics and Metabolism

DIURIL is not metabolized but is eliminated rapidly by the kidney; 96 percent of an intravenous dose is excreted unchanged in the urine within 23 hours. The plasma half-life of chlorothiazide is 45 to 120 minutes. Chlorothiazide crosses the placental but not the blood-brain barrier and is excreted in breast milk.

INDICATIONS AND USAGE

Intravenous Sodium DIURIL is indicated as adjunctive therapy in edema associated with congestive heart failure, hepatic cirrhosis, and corticosteroid and estrogen therapy.

Intravenous Sodium DIURIL has also been found useful in edema due to various forms of renal dysfunction such as nephrotic syndrome, acute glomerulonephritis, and chronic renal failure.

Use in Pregnancy

Routine use of diuretics during normal pregnancy is inappropriate and exposes mother and fetus to unnecessary hazard. Diuretics do not prevent development of toxemia of pregnancy and there is no satisfactory evidence that they are useful in the treatment of toxemia.

Edema during pregnancy may arise from pathologic causes or from the physiologic and mechanical consequences of pregnancy. Thiazides are indicated in pregnancy when edema is due to pathologic causes, just as they are in the absence of pregnancy (see PRECAUTIONS, Pregnancy). Dependent edema in pregnancy, resulting from restriction of venous return by the gravid uterus, is properly treated through elevation of the lower extremities and use of support stockings. Use of diuretics to lower intravas-cular volume in this instance is illogical and unnecessary. During normal pregnancy there is hypervolemia which is not harmful to the fetus or the mother in the absence of cardiovascular disease. However, it may be associated with edema, rarely generalized edema. If such edema causes discomfort, increased recumbency will often provide relief. Rarely this edema may cause extreme discomfort which is not relieved by rest. In these instances, a short course of diuretic therapy may provide relief and be appropriate.

CONTRAINDICATIONS

Anuria.

Hypersensitivity to any component of this product or to other sulfonamide-derived drugs.

WARNINGS

Intravenous use in infants and children has been limited and is not generally recommended.

Use with caution in severe renal disease. In patients with renal disease, thiazides may precipitate azotemia. Cumulative effects of the drug may develop in patients with impaired renal function.

Thiazides should be used with caution in patients with impaired hepatic function or progressive liver disease, since minor alterations of fluid and electrolyte balance may precipitate hepatic coma.

Thiazides may add to or potentiate the action of other antihypertensive drugs.

Sensitivity reactions may occur in patients with or without a history of allergy or bronchial asthma.

The possibility of exacerbation or activation of systemic lupus erythematosus has been reported.

Lithium generally should not be given with diuretics (see PRECAUTIONS, Drug Interactions).

PRECAUTIONS

General

All patients receiving diuretic therapy should be observed for evidence of fluid or electrolyte imbalance: namely, hyponatremia, hypochloremic alkalosis, and hypokalemia. Serum and urine electrolyte determinations are particularly important when the patient is vomiting excessively or receiving parenteral fluids. Warning signs or symptoms of fluid and electrolyte imbalance, irrespective of cause, include dryness of mouth, thirst, weakness, lethargy, drowsiness, restlessness, confusion, seizures, muscle pains or cramps, muscular fatigue, hypotension, oliguria, tachycardia, and gastrointestinal disturbances such as nausea and vomiting.

Hypokalemia may develop especially with brisk diuresis, when severe cirrhosis is present or after prolonged therapy.

Interference with adequate oral electrolyte intake will also contribute to hypokalemia. Hypokalemia may cause cardiac arrhythmias and may also sensitize or exaggerate the response of the heart to the toxic effects of digitalis (e.g., increased ventricular irritability). Hypokalemia may be avoided or treated by use of potassium-sparing diuretics or potassium supplements such as foods with a high potassium content.

Although any chloride deficit is generally mild and usually does not require specific treatment except under extraordinary circumstances (as in liver disease or renal disease), chloride replacement may be required in the treatment of metabolic alkalosis.

Dilutional hyponatremia may occur in edematous patients in hot weather; appropriate therapy is water restriction, rather than administration of salt, except in rare instances when the hyponatremia is life-threatening. In actual salt depletion, appropriate replacement is the therapy of choice.

Hyperuricemia may occur or acute gout may be precipitated in certain patients receiving thiazides.

In diabetic patients dosage adjustments of insulin or oral hypoglycemic agents may be required. Hyperglycemia may occur with thiazide diuretics. Thus latent diabetes mellitus may become manifest during thiazide therapy.

The antihypertensive effects of the drug may be enhanced in the postsympathectomy patient.

If progressive renal impairment becomes evident, consider withholding or discontinuing diuretic therapy.

Thiazides have been shown to increase the urinary excretion of magnesium; this may result in hypo-magnesemia.

Thiazides may decrease urinary calcium excretion. Thiazides may cause intermittent and slight elevation of serum calcium in the absence of known disorders of calcium metabolism. Marked hypercalcemia may be evidence of hidden hyperparathyroidism. Thiazides should be discontinued before carrying out tests for parathyroid function.

Increases in cholesterol and triglyceride levels may be associated with thiazide diuretic therapy.

Laboratory Tests

Periodic determination of serum electrolytes to detect possible electrolyte imbalance should be done at appropriate intervals.

Drug Interactions

When given concurrently the following drugs may interact with thiazide diuretics.

Alcohol, barbiturates, or narcotics - potentiation of orthostatic hypotension may occur.
Antidiabetic drugs - (oral agents and insulin) - dosage adjustment of the antidiabetic drug may be required.
Other antihypertensive drugs - additive effect or potentiation.
Corticosteroids, ACTH - intensified electrolyte depletion, particularly hypokalemia.
Pressor amines (e.g., norepinephrine) - possible decreased response to pressor amines but not sufficient to preclude their use.
Skeletal muscle relaxants, nondepolarizing (e.g., tubocurarine) - possible increased responsiveness to the muscle relaxant.
Lithium - generally should not be given with diuretics. Diuretic agents reduce the renal clearance of lithium and add a high risk of lithium toxicity. Refer to the package insert for lithium preparations before use of such preparations with Sodium DIURIL.
Non-steroidal Anti-inflammatory Drugs - In some patients, the administration of a non-steroidal anti-inflammatory agent can reduce the diuretic, natriuretic, and antihypertensive effects of loop, potassium-sparing and thiazide diuretics. Therefore, when Sodium DIURIL and non-steroidal anti-inflammatory agents are used concomitantly, the patient should be observed closely to determine if the desired effect of the diuretic is obtained.

Drug/Laboratory Test Interactions

Thiazides should be discontinued before carrying out tests for parathyroid function (see PRECAUTIONS, General).

Carcinogenesis, Mutagenesis, Impairment of Fertility

Carcinogenicity studies have not been conducted with chlorothiazide.

Chlorothiazide was not mutagenic in vitro in the Ames microbial mutagen test (using a maximum concentration of 5 mg/plate and Salmonella typhimurium strains TA98 and TA100) and was not mutagenic and did not induce mitotic nondisjunction in diploid-strains of Aspergillus nidulans.

Chlorothiazide had no adverse effects on fertility in female rats at doses up to 60 mg/kg/day and no adverse effects on fertility in male rats at doses up to 40 mg/kg/day. These doses are 1.5 and 1.0 times** the recommended maximum human dose, respectively, when compared on a body weight basis.

Pregnancy

TERATOGENIC EFFECTS

Teratogenic Effects: Although reproduction studies performed with chlorothiazide doses of 50 mg/kg/day in rabbits, 60 mg/kg/day in rats and 500 mg/kg/day in mice revealed no external abnormalities of the fetus or impairment of growth and survival of the fetus due to chlorothiazide, such studies did not include complete examinations for visceral and skeletal abnormalities. It is not known whether chlorothiazide can cause fetal harm when administered to a pregnant woman; however, thiazides cross the placental barrier and appear in cord blood. DIURIL should be used during pregnancy only if clearly needed (see INDICATIONS AND USAGE).

NONTERATOGENIC EFFECTS

Nonteratogenic Effects: Chlorothiazide may cause fetal or neonatal jaundice, thrombocytopenia, and possibly other adverse reactions which have occurred in the adult.

Nursing Mothers

Because of the potential for serious adverse reactions in nursing infants from Intravenous Sodium DIURIL, a decision should be made whether to discontinue nursing or to discontinue the drug, taking into account the importance of the drug to the mother.

Pediatric Use

Safety and effectiveness of Intravenous Sodium DIURIL in pediatric patients have not been established.

Geriatric Use

Clinical studies of Intravenous Sodium DIURIL did not include sufficient numbers of subjects aged 65 and over to determine whether they respond differently from younger subjects. Other reported clinical experience has not identified differences in responses between the elderly and younger patients. In general, dose selection for an elderly patient should be cautious, usually starting at the low end of the dosing range, reflecting the greater frequency of decreased hepatic, renal, or cardiac function, and of concomitant disease or other drug therapy.

This drug is known to be substantially excreted by the kidney, and the risk of toxic reactions to this drug may be greater in patients with impaired renal function. Because elderly patients are more likely to have decreased renal function, care should be taken in dose selection, and it may be useful to monitor renal function (see WARNINGS).

ADVERSE REACTIONS

The following adverse reactions have been reported and, within each category, are listed in order of decreasing severity.

Body as a Whole: Weakness.
Cardiovascular: Hypotension including orthostatic hypotension (may be aggravated by alcohol, barbiturates, narcotics or antihypertensive drugs).
Digestive: Pancreatitis, jaundice (intrahepatic cholestatic jaundice), diarrhea, vomiting, sialadenitis, cramping, constipation, gastric irritation, nausea, anorexia.
Hematologic: Aplastic anemia, agranulocytosis, leukopenia, hemolytic anemia, thrombocytopenia.
Hypersensitivity: Anaphylactic reactions, necrotizing angiitis (vasculitis and cutaneous vasculitis), respiratory distress including pneumonitis and pulmonary edema, photosensitivity, fever, urticaria, rash, purpura.
Metabolic: Electrolyte imbalance (see PRECAUTIONS), hyperglycemia, glycosuria, hyperuricemia.
Musculoskeletal: Muscle spasm.
Nervous System/Psychiatric: Vertigo, paresthesias, dizziness, headache, restlessness.
Skin: Erythema multiforme including Stevens-Johnson syndrome, exfoliative dermatitis including toxic epidermal necrolysis, alopecia.
Special Senses: Transient blurred vision, xanthopsia.
Renal: Renal failure, renal dysfunction, interstitial nephritis, (see WARNINGS); hematuria (following intravenous use).
Urogenital: Impotence.

Whenever adverse reactions are moderate or severe, thiazide dosage should be reduced or therapy withdrawn.

To report SUSPECTED ADVERSE REACTIONS, contact Oak Pharmaceuticals, Inc. at 1-800-932-5676 or FDA at 1-800-FDA-1088 or www.fda.gov/medwatch.

OVERDOSAGE

The most common signs and symptoms observed are those caused by electrolyte depletion (hypokalemia, hypochloremia, hyponatremia) and dehydration resulting from excessive diuresis. If digitalis has also been administered, hypokalemia may accentuate cardiac arrhythmias.

In the event of overdosage, symptomatic and supportive measures should be employed. Correct dehydration, electrolyte imbalance, hepatic coma and hypotension by established procedures. If required, give oxygen or artificial respiration for respiratory impairment.

The degree to which chlorothiazide sodium is removed by hemodialysis has not been established.

The intravenous LD50 of chlorothiazide in the mouse is 1.1 g/kg.

DOSAGE AND ADMINISTRATION

Intravenous Sodium DIURIL should be reserved for patients unable to take oral medication or for emergency situations.

Therapy should be individualized according to patient response. Use the smallest dosage necessary to achieve the required response.

Intravenous use in infants and children has been limited and is not generally recommended.

When medication can be taken orally, therapy with DIURIL tablets or oral suspension may be substituted for intravenous therapy, using the same dosage schedule as for the parenteral route.

Intravenous Sodium DIURIL may be given slowly by direct intravenous injection or by intravenous infusion.

Extravasation must be rigidly avoided. Do not give subcutaneously or intramuscularly.

The usual adult dosage is 0.5 to 1 g once or twice a day. Many patients with edema respond to intermittent therapy, i.e., administration on alternate days or on three to five days each week. With an intermittent schedule, excessive response and the resulting undesirable electrolyte imbalance are less likely to occur.

Directions for Reconstitution

Use aseptic technique. Because Intravenous Sodium DIURIL contains no preservative, a fresh solution should be prepared immediately prior to each administration, and the unused portion should be discarded.

Add 18 mL of Sterile Water for Injection to the vial to form an isotonic solution for intravenous injection. Never add less than 18 mL. When reconstituted with 18 mL of Sterile Water, the final concentration of Intravenous Sodium DIURIL is 28 mg/mL. The reconstituted solution is clear and essentially free from visible particles. Parenteral drug products should be inspected visually for particulate matter and discoloration prior to use whenever solution and container permit. The solution is compatible with dextrose or sodium chloride solutions for intravenous infusion. Avoid simultaneous administration of solutions of chlorothiazide with whole blood or its derivatives.

HOW SUPPLIED

Intravenous Sodium DIURIL is a dry, sterile lyophilized white powder usually in plug form, supplied in vials containing chlorothiazide sodium equivalent to 0.5 g of chlorothiazide.

NDC 76478-711-40.

Storage

Store at 20° to 25°C (68° to 77°F). See USP Controlled Room Temperature.

For single dose only. Use solution immediately after reconstitution (see DOSAGE AND ADMINISTRATION, Directions for Reconstitution). Discard unused portion of the reconstituted solution.

** Calculations based on a human body weight of 50 kg.

AKORN

Distributed by:
Akorn Operating Company LLC
Gurnee, IL 60031

® Registered trademark of Merck & Co., Inc.
Whitehouse Station, NJ 08889, U.S.A.

OPCH00N Rev. 03/22

Principal Display Panel Text for Container Label:

NDC 76478-711-40 Single Dose Vial

Intravenous

Sodium Diuril®

(chlorothiazide sodium)

0.5 g

Chlorothiazide Equivalent

Rx only Akorn Logo

Principal Display Panel Text for Carton Label:

NDC 76478-711-40 Single
Dose Vial

Intravenous

Sodium Diuril®
(chlorothiazide sodium)

0.5 g

Chlorothiazide Equivalent

For Preparation of Intravenous

Solutions

Rx only Akorn Logo